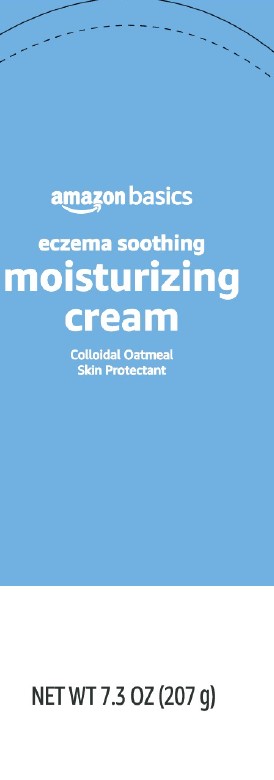 DRUG LABEL: Colloidal oatmeal
NDC: 72288-965 | Form: CREAM
Manufacturer: Amazon.com Services LLC
Category: otc | Type: HUMAN OTC DRUG LABEL
Date: 20250207

ACTIVE INGREDIENTS: OATMEAL 10.4 mg/1 g
INACTIVE INGREDIENTS: WATER; GLYCERIN; DISTEARYLDIMONIUM CHLORIDE; PETROLATUM; ISOPROPYL PALMITATE; CETYL ALCOHOL; DIMETHICONE; PANTHENOL; OAT KERNEL OIL; STEARETH-20; BENZALKONIUM CHLORIDE; CERAMIDE 3; SODIUM CHLORIDE; BENZYL ALCOHOL; SODIUM HYDROXIDE

Basics 965.001/965AC
Eczema Soothing Moisturizing Cream

Claims

The basic idea: highly rated products at low prices.

Active ingredient

Colloidal oatmeal 1%

Purpose

Skin protectant

Uses

temporarily protects and helps relieve minor skin irritation and itching due to:

- eczema
- rashes

Warnings

For external use only

When using this product

- do not get into eyes

Stop use and ask a doctor if

- condition worsens
- symptoms last more than 7 days or clear up and occur again withing a few days

Keep out of reach of children.

If swallowed, get medical help or contact a Poison Control Center right away.

Directions

apply as needed

Inactive ingredients

water, glycerin, distearyldimonium chloride, petrolatum, isopropyl palmitate, cetyl alcohol, dimethicone, panthenol, Avena sativa (oat) kernel oil, steareth-20, benzalkonium chloride, ceramide NP, sodium chloride, benzyl alcohol, sodium hydroxide

ADVERSE REACTIONS

DISTRIBUTED BY: Amazon.com Services LLC

Seattle, WA 98109 1-877-485-0385

amazon

©2024 Amazon.com, Inc. or its affilates.

All rights reserved.

www.amazon.com/amazonbasics

principal panel display

amazon basics

eczema soothing

moisturizing

cream

Colloidal Oatmeal

Skin Protectant

NET WT 7.3 OZ (207 g)